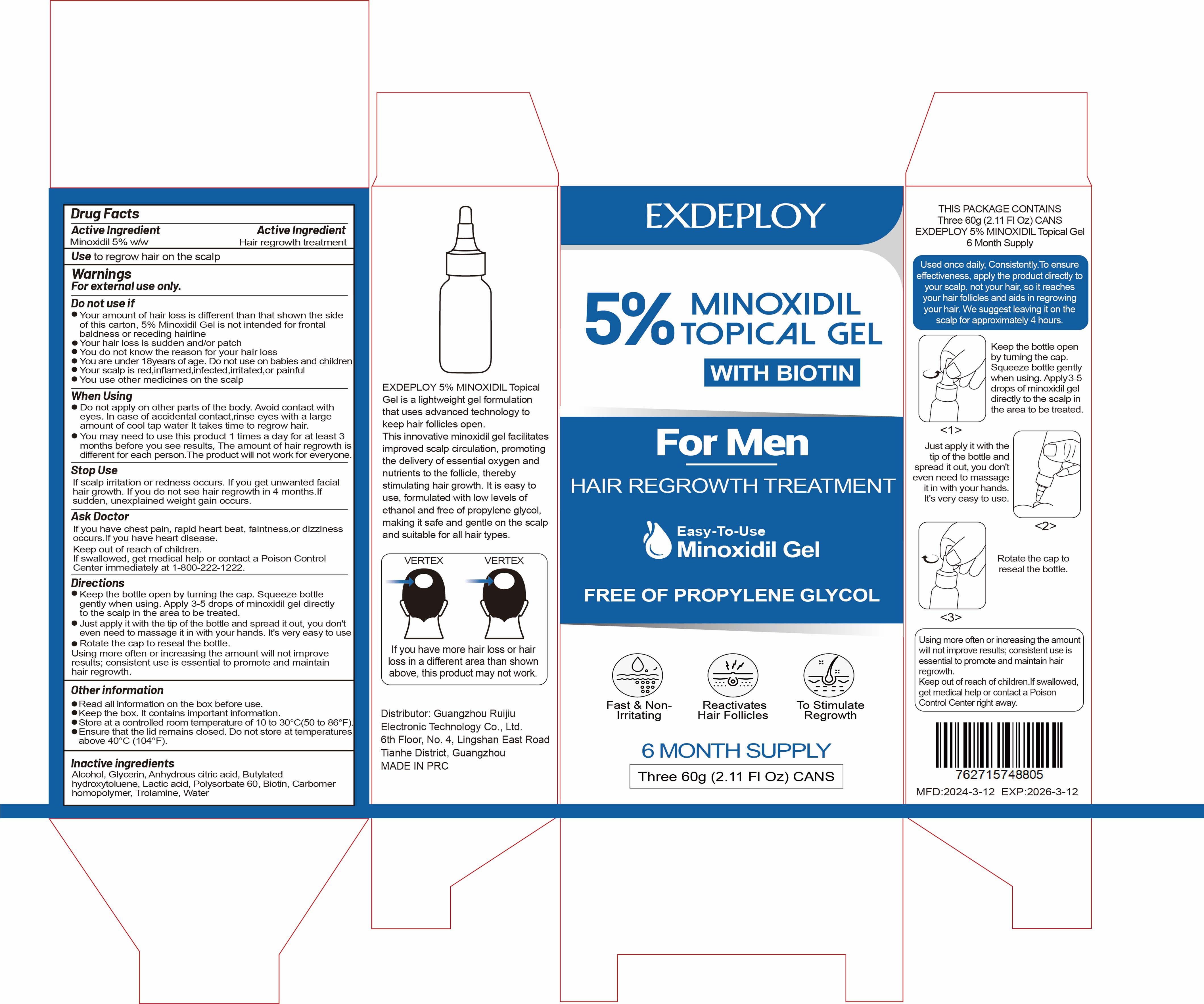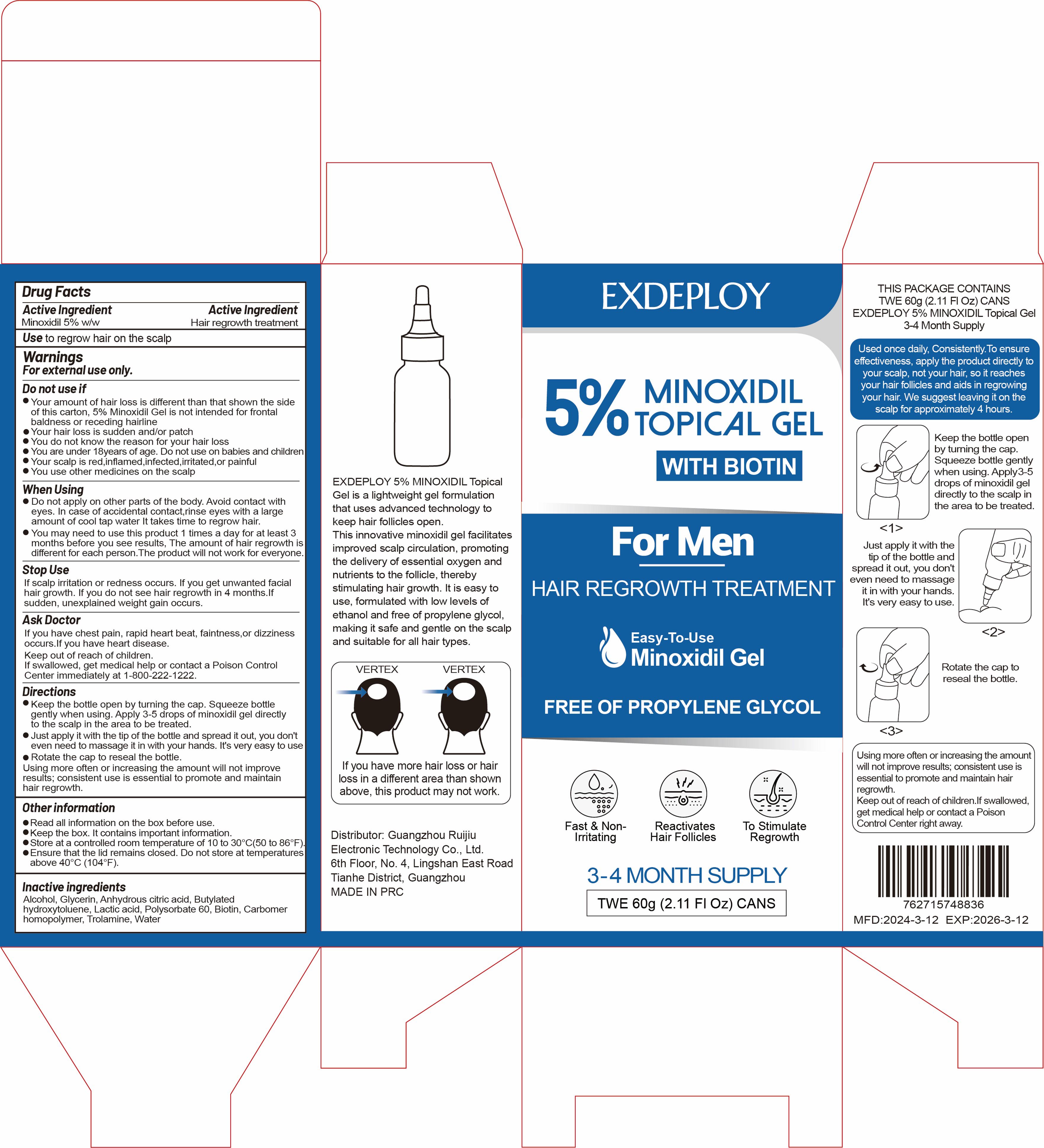 DRUG LABEL: EXDEPLOY 5% Minoxidil Topical Gel
NDC: 83767-201 | Form: GEL
Manufacturer: Guangzhou Ruijiu Electronic Technology Co., Ltd.
Category: otc | Type: HUMAN OTC DRUG LABEL
Date: 20240409

ACTIVE INGREDIENTS: MINOXIDIL 5 g/100 g
INACTIVE INGREDIENTS: ALCOHOL; LACTIC ACID; POLYSORBATE 60; WATER; BIOTIN; GLYCERIN; CARBOMER HOMOPOLYMER, UNSPECIFIED TYPE; TROLAMINE; ANHYDROUS CITRIC ACID; BUTYLATED HYDROXYTOLUENE

EXDEPLOY 5% MINOXIDIL TOPICAL GEL

EXDEPLOY 5% MINOXIDIL TOPICAL GEL

ACTIVE INGREDIENT

Minoxidil 5%

PURPOSE

Hair regrowth treatment

INDICATIONS AND USAGE

to regrow hair on the scalp

WARNINGS

For externaluse only.

DO NOT USE

Your amount of hair loss is different than that shown the side of this carton, 5% Minoxidil Gel is not intended for fronta baldness or receding hairline.
Your hair loss is sudden and/or patch.
You do not know the reason for your hair loss.
You are under 18years of age. Do not use on babies and children.
Your scalp is red,inflamed,infected,irritated,or painful.
You use other medicines on the scalp.

WHEN USING

Do not apply on other parts of the body. Avoid contact with eyes.In case of accidental contact,rinse eyes with a large amount of cool tap water lt takes time to regrow hair.
You may need to use this product 1 times a day for at least 3 months before you see results, The amount of hair regrowth is different for each person.The product will not work for everyone.

STOP USE

lf scalp irritation or redness occurs. If you get unwanted facialhair growth. lf you do not see hair regrowth in 4 months.lfsudden, unexplained weight gain occurs.

Keep out of reach of children.
If swallowed, get medical help or contact a Poison Control Center immediately at 1-800-222-1222

DOSAGE AND ADMINISTRATION

Keep the bottle open by turning the cap. Squeeze bottlegently when using. Apply 3-5 drops of minoxidil gel directlyto the scalp in the area to be treated.
Just apply it with the tip of the bottle and spread it out, you don't
even need to massage it in with your hands. lt's very easy to use.
Rotate the cap to reseal the bottle.
Using more often or increasing the amount will not improveresults; consistent use is essential to promote and maintainhair regrowth.

STORAGE AND HANDLING

Read all information on the box before use.
Keep the box. It contains important information.
Store at a controlled room temperature of 10 to 30°C(50 to 86°F).
Ensure that the lid remains closed. Do not store at temperatures above 40°C(104°F).

INACTIVE INGREDIENT

Alcohol
Glycerin
Anhydrous citric acid
Butylated hydroxytoluene
Lactic acid
Polysorbate 60
Biotin
Carbomer homopolymer
Trolamine
Water